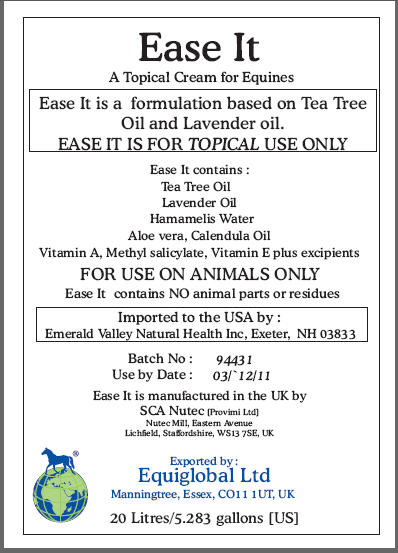 DRUG LABEL: Ease It
NDC: 52338-744 | Form: CREAM
Manufacturer: SCA NuTec
Category: animal | Type: PRESCRIPTION ANIMAL DRUG LABEL
Date: 20100419

ACTIVE INGREDIENTS: TEA TREE OIL 10 mg/1 mL; LAVENDER OIL 5 mg/1 mL; WITCH HAZEL 10 mg/1 mL; ALOE VERA LEAF 15 mg/1 mL; CALENDULA OFFICINALIS FLOWER 5 mg/1 mL; VITAMIN A 1000 [iU]/1 mL; METHYL SALICYLATE 10 mg/1 mL; VITAMIN E 4650 mg/1 mL

Ease It

A Topical Cream for Equines

Ease It is a formulation based on Tea Tree
Oil and Lavender oil.
EASE IT IS FOR TOPICAL USE ONLY

Ease It contains :
Tea Tree Oil
Lavender Oil
Hamamelis Water
Aloe vera, Calendula Oil
Vitamin A, Methyl salicylate, Vitamin E plus excipients

WARNINGS

FOR USE ON ANIMALS ONLY

Ease It contains NO animal parts or residues

Imported to the USA by :
Emerald Valley Natural Health Inc, Exeter, NH 03833
Batch No: 94431
Use by Date : 03/12/11
Ease It is manufactured in the UK by
SCA Nutec [Provimi Ltd]
Nutec Mill, Eastern Avenue
Lichfield, Staffordshire, WS13 7SE, UK
Exported by :
Equiglobal Ltd
Manningtree, Essex, CO11 1UT, UK
20 Litres/5.283 gallons [US]